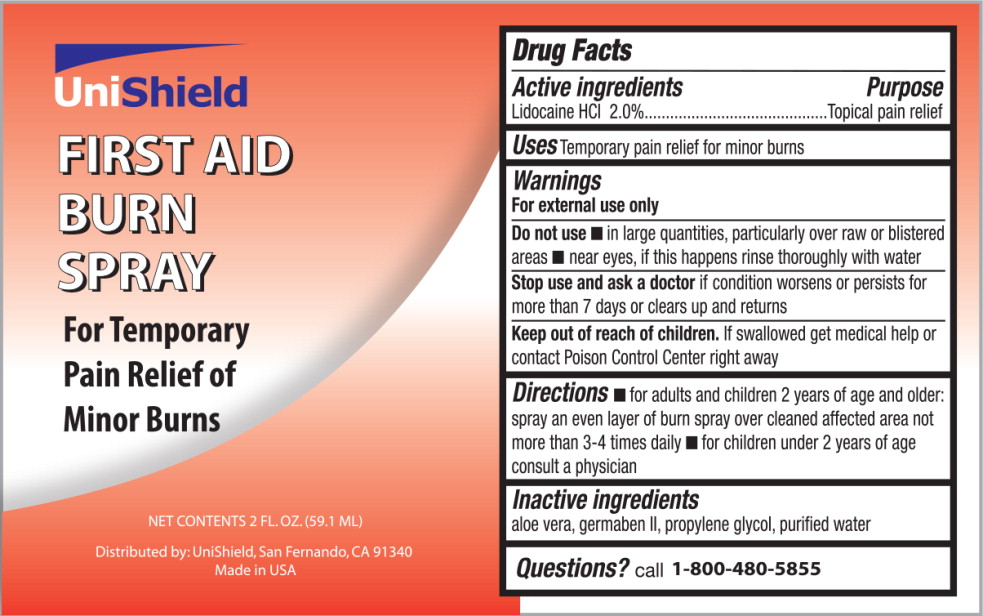 DRUG LABEL: First Aid Burn
NDC: 49314-5100 | Form: SPRAY
Manufacturer: Unishield 
Category: otc | Type: HUMAN OTC DRUG LABEL
Date: 20191007

ACTIVE INGREDIENTS: Lidocaine Hydrochloride 20 g/1000 mL
INACTIVE INGREDIENTS: aloe vera leaf; propylene glycol; diazolidinyl urea; water

Drug Facts

Active ingredients

Lidocaine HCl 2.0%

Purpose

Topical pain relief

Uses

Temporary pain relief for minor burns

Warnings

For external use only

Do not use

- in large quantities, particularly over raw or blistered areas
- near eyes, if this happens rinse thoroughly with water

Stop use and ask a doctor if condition worsens or persists for more than 7 days or clears up and returns

Keep out of reach of children. If swallowed get medical help or contact Poison Control Center right away

Directions

- for adults and children 2 years of age and older: spray an even layer of burn spray over cleaned affected area not more than 3-4 times daily
- for children under 2 years of age consult a physician

Inactive ingredients

aloe vera, germaben II, propylene glycol, purified water

Questions?

call 1-800-480-5855

Principal Display Panel - 59.1 mL Bottle Label

UniShield

FIRST AID
BURN
SPRAY

For Temporary
Pain Relief of
Minor Burns

NET CONTENTS 2 FL.OZ. (59.1 ML)

Distributed by: UniShield, San Fernando, CA 91340
Made in USA